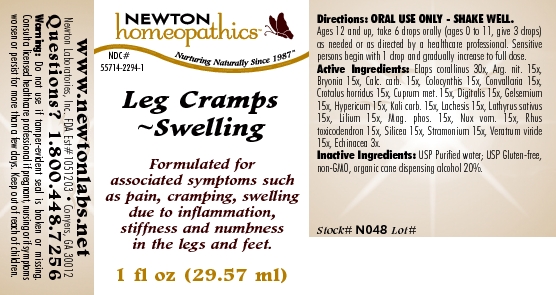 DRUG LABEL: Leg Cramps - Swelling 
NDC: 55714-2294 | Form: LIQUID
Manufacturer: Newton Laboratories, Inc.
Category: homeopathic | Type: HUMAN OTC DRUG LABEL
Date: 20110301

ACTIVE INGREDIENTS: Micrurus Corallinus Venom 30 [hp_X]/1 mL; Silver Nitrate 15 [hp_X]/1 mL; Bryonia Alba Root 15 [hp_X]/1 mL; Oyster Shell Calcium Carbonate, Crude 15 [hp_X]/1 mL; Citrullus Colocynthis Fruit Pulp 15 [hp_X]/1 mL; Convallaria Majalis 15 [hp_X]/1 mL; Crotalus Horridus Horridus Venom 15 [hp_X]/1 mL; Copper 15 [hp_X]/1 mL; Digitalis 15 [hp_X]/1 mL; Gelsemium Sempervirens Root 15 [hp_X]/1 mL; Hypericum Perforatum 15 [hp_X]/1 mL; Potassium Carbonate 15 [hp_X]/1 mL; Lachesis Muta Venom 15 [hp_X]/1 mL; Lathyrus Sativas Seed 15 [hp_X]/1 mL; Lilium Lancifolium Whole Flowering 15 [hp_X]/1 mL; Magnesium Phosphate, Dibasic Trihydrate 15 [hp_X]/1 mL; Strychnos Nux-vomica Seed 15 [hp_X]/1 mL; Toxicodendron Pubescens Leaf 15 [hp_X]/1 mL; Silicon Dioxide 15 [hp_X]/1 mL; Datura Stramonium 15 [hp_X]/1 mL; Veratrum Viride Root 15 [hp_X]/1 mL; Echinacea, Unspecified 3 [hp_X]/1 mL
INACTIVE INGREDIENTS: Alcohol

Leg Cramps - Swelling

INDICATIONS & USAGE SECTION

Leg Cramps - Swelling Formulated for associated symptoms such as pain, cramping, swelling due to inflammation, stiffness and numbness in the legs and feet.

DOSAGE & ADMINISTRATION SECTION

Directions: ORAL USE ONLY - SHAKE WELL. Ages 12 and up, take 6 drops orally (ages 0 to 11, give 3 drops) as needed or as directed by a healthcare professional. Sensitive persons begin with 1 drop and gradually increase to full dose.

OTC - ACTIVE INGREDIENT SECTION

Elaps corallinus 30x, Arg. nit. 15x, Bryonia 15x, Calc. carb. 15x, Colocynthis 15x, Convallaria 15x, Crotalus horridus 15x, Cuprum met. 15x, Digitalis 15x, Gelsemium 15x, Hypericum 15x, Kali carb. 15x, Lachesis 15x, Lathyrus sativus 15x, Lilium 15x, Mag. phos. 15x, Nux vom. 15x, Rhus toxicodendron 15x, Silicea 15x, Stramonium 15x, Veratrum viride 15x, Echinacea 3x.

OTC - PURPOSE SECTION

Formulated for associated symptoms such as pain, cramping, swelling due to inflammation, stiffness and numbness in the legs and feet.

INACTIVE INGREDIENT SECTION

Inactive Ingredients: USP Purified Water; USP Gluten-free, non-GMO, organic cane dispensing alcohol 20%.

QUESTIONS SECTION

www.newtonlabs.net Newton Laboratories, Inc. FDA Est # 1051203 - Conyers, GA 30012
Questions? 1.800.448.7256

WARNINGS SECTION

Warning: Do not use if tamper - evident seal is broken or missing. Consult a licensed healthcare professional if pregnant, nursing or if symptoms worsen or persist for more than a few days. Keep out of reach of children.

OTC - PREGNANCY OR BREAST FEEDING SECTION

Consult a licensed healthcare professional if pregnant, nursing or if symptoms worsen or persist for more than a few days.

OTC - KEEP OUT OF REACH OF CHILDREN SECTION

Keep out of reach of children.